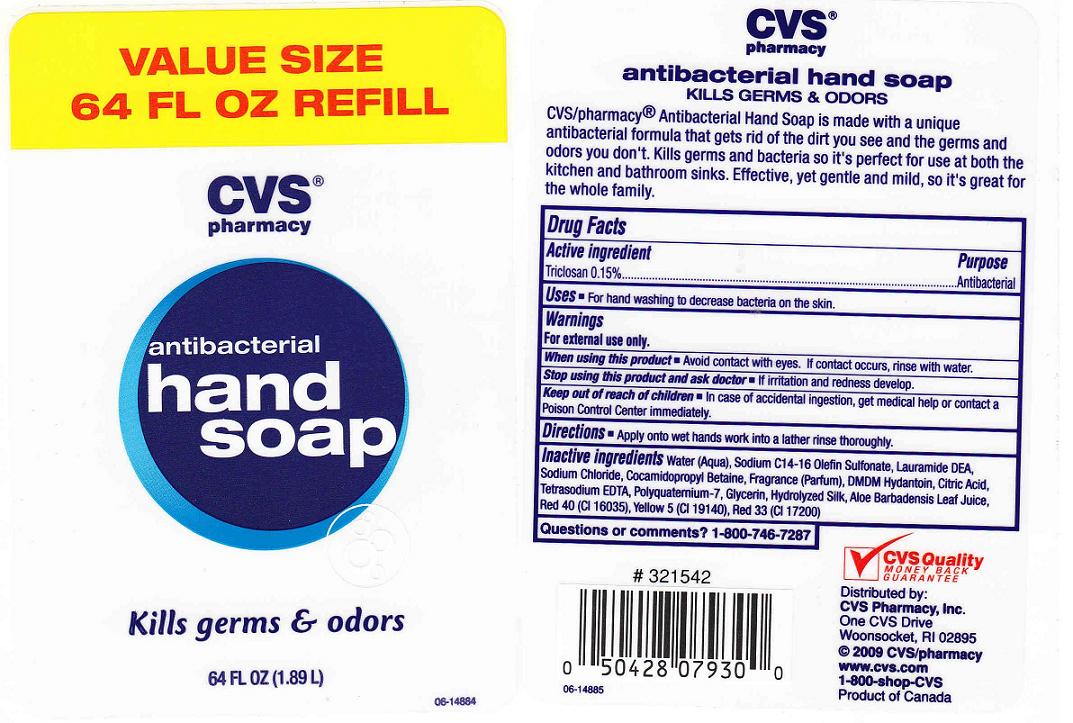 DRUG LABEL: Antibacterial Hand 
NDC: 59779-216 | Form: SOAP
Manufacturer: CVS Pharmacy
Category: otc | Type: HUMAN OTC DRUG LABEL
Date: 20100706

ACTIVE INGREDIENTS: TRICLOSAN 0.1500 mL/100.0000 mL

DRUG FACTS BOX - BACK LABEL

Active Ingredient

Triclosan 0.15% (Anitbacterial)

Uses and Directions

- Uses: For hand washing to decrease bacteria on the skin.
- Directions: Apply onto wet hands work into a lather rinse thoroughly.

Warnings

For external use only.

When using this product

Avoid contact with eyes. If contact occurs, rinse with water.

Stop using this product and ask doctor

If irritation and redness develop.

Keep out of reach of children

In case of accidental ingestion, get medical help or contact a Poison Control Center immediately.

PACKAGE LABEL

- 64OZ FRONT AND BACK LABELS: cvs64.jpg